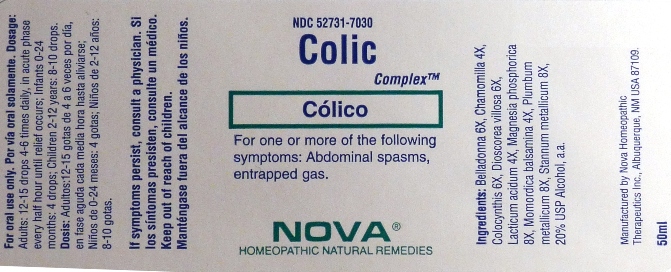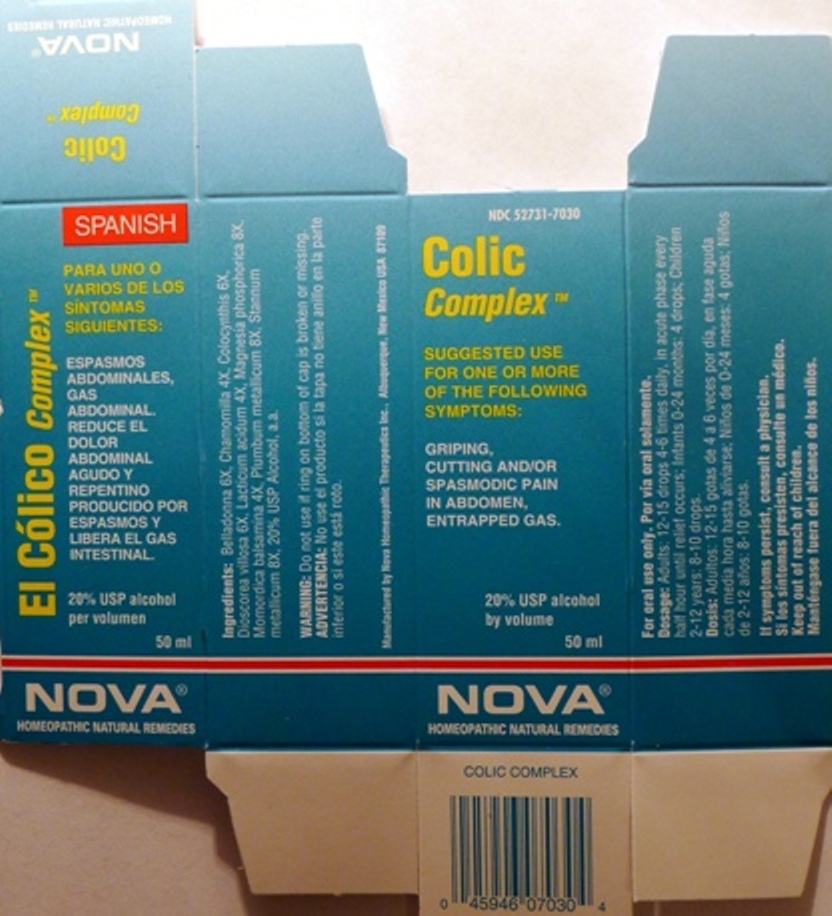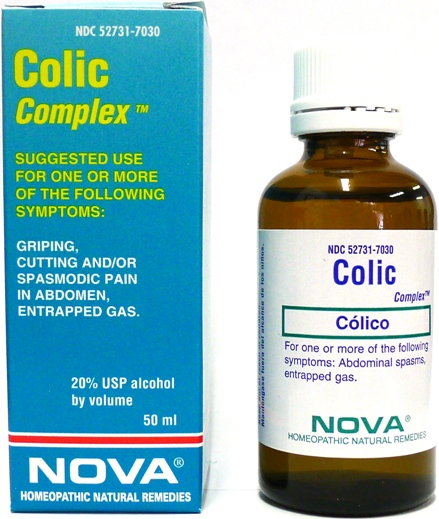 DRUG LABEL: Colic Complex
NDC: 52731-7030 | Form: LIQUID
Manufacturer: Nova Homeopathic Therapeutics, Inc.
Category: homeopathic | Type: HUMAN OTC DRUG LABEL
Date: 20110601

ACTIVE INGREDIENTS: ATROPA BELLADONNA 6 [hp_X]/1 mL; MATRICARIA RECUTITA 4 [hp_X]/1 mL; CITRULLUS COLOCYNTHIS FRUIT PULP 6 [hp_X]/1 mL; DIOSCOREA VILLOSA ROOT 6 [hp_X]/1 mL; LACTIC ACID, DL- 4 [hp_X]/1 mL; MAGNESIUM PHOSPHATE, DIBASIC TRIHYDRATE 8 [hp_X]/1 mL; MOMORDICA BALSAMINA IMMATURE FRUIT 4 [hp_X]/1 mL; LEAD 8 [hp_X]/1 mL; TIN 8 [hp_X]/1 mL
INACTIVE INGREDIENTS: ALCOHOL

Colic Complex

Purpose:

Suggested use for one or more of the following symptoms:

Abdominal spasms, entrapped gas.

Usage and Dosage:

For oral use only.

DOSAGE AND ADMINISTRATION

Adults:
In Acute Phase:
12-15 drops, every half hour until relief occurs
When Relief Occurs:
12-15 drops, 4-6 times daily
Children 2-12 years:
8-10 drops, 4-6 times daily
Infants 0-24 months:
4 drops, 4-6 times daily

Warnings:

Keep out of reach of children.

WARNINGS

If symptoms persist, consult a physician.
Do not use if ring on bottom of cap is broken or missing.

Active Ingredients:

Belladonna 6X, Chamomilla 4X, Colocynthis 6X, Dioscorea villosa 6X, Lacticum acidum 4X, Magnesia phosphorica 8X, Momordica balsamina 4X, Plumbum metallicum 8X, Stannum metallicum 8X

Inactive Ingredients:

Alcohol, 20% USP

QUESTIONS

Manufactured by Nova Homeopathic Therapeutics Inc., Albuquerque, New Mexico USA 87109
1-800-225-8094

PACKAGE LABEL

Colic Complex Product

Colic Complex Bottle Label

Colic Complex Box